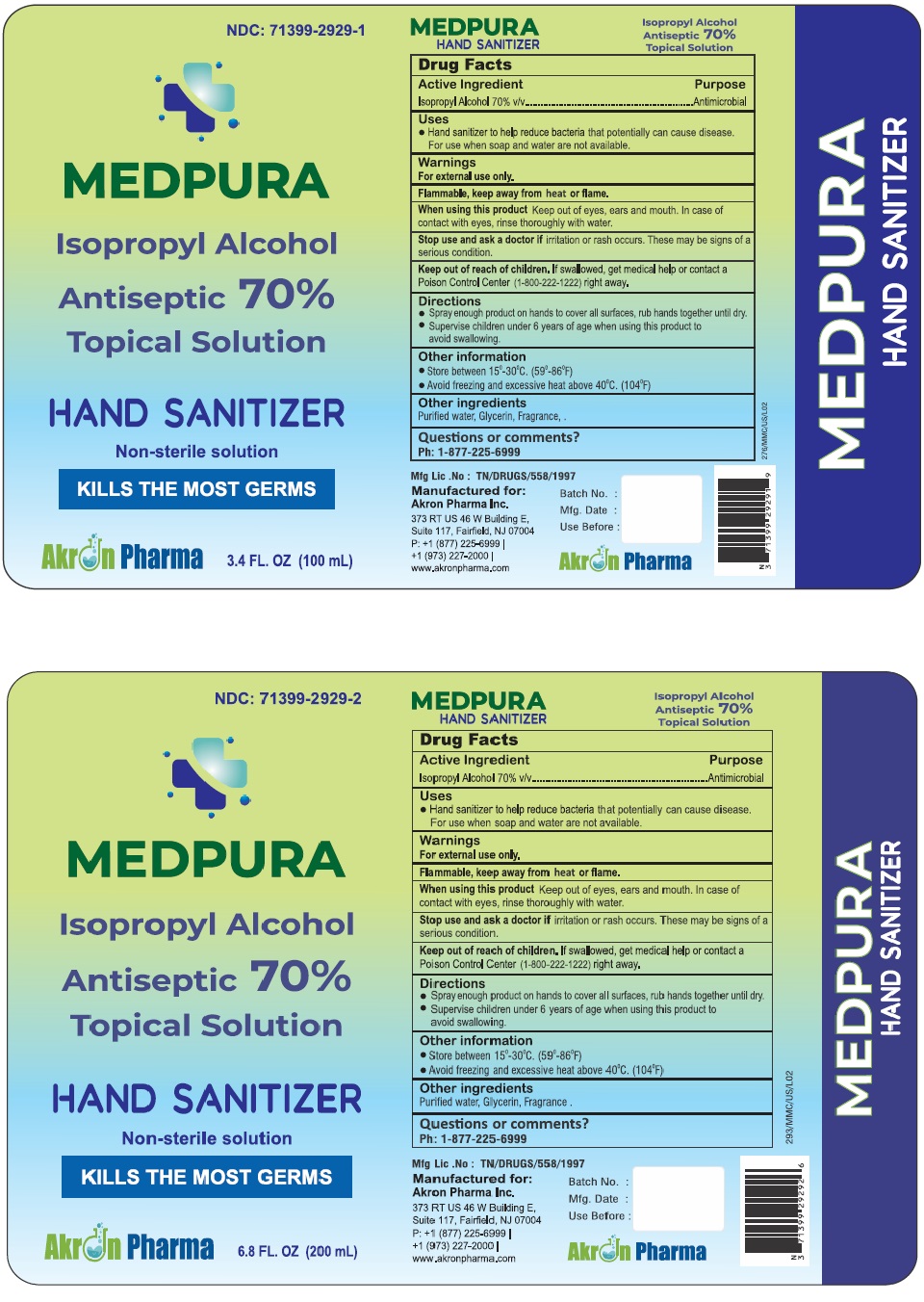 DRUG LABEL: MEDPURA Hand Sanitizer Topical Solution
NDC: 71399-2929 | Form: SOLUTION
Manufacturer: Akron Pharma Inc
Category: otc | Type: HUMAN OTC DRUG LABEL
Date: 20210518

ACTIVE INGREDIENTS: ISOPROPYL ALCOHOL 70 mL/100 mL
INACTIVE INGREDIENTS: WATER; GLYCERIN

MEDPURA Hand Sanitzer Topical Solution
Non-sterile

Active Ingredient(s)

Isopropyl Alcohol 70% v/v.

Purpose

Antimicrobial

Use

Hand Sanitizer to help reduce bacteria that potentially can cause disease. For use when soap and water are not available.

Warnings

For external use only. Flammable. Keep away from heat or flame

Do not use

- in children less than 2 months of age
- on open skin wounds

When using this product keep out of eyes, ears, and mouth. In case of contact with eyes, rinse thoroughly with water.

Stop use and ask a doctor if irritation or rash occurs. These may be signs of a serious condition.

Keep out of reach of children. If swallowed, get medical help or contact a Poison Control Center (1-800-222-1222) right away.

Directions

- Place enough product on hands to cover all surfaces. Rub hands together until dry.
- Supervise children under 6 years of age when using this product to avoid swallowing.

Other information

- Store between 15^0-30^0C (59^0-86^0F)
- Avoid freezing and excessive heat above 40^0C (104^0F)

Inactive ingredients

Purified water, Glycerin, Fragrance

Questions or comments?

Ph: 1-877-225-6999

Mfg Lic. No: TN/DRUGS/558/1997

Manufactured for:

Akron Pharma Inc.

373 RT US 46W Building E,

Suite 117, Fairfield, NJ 07004

P: +1(877) 225-6999

+1(973) 227-2000

www.akronpharma.com